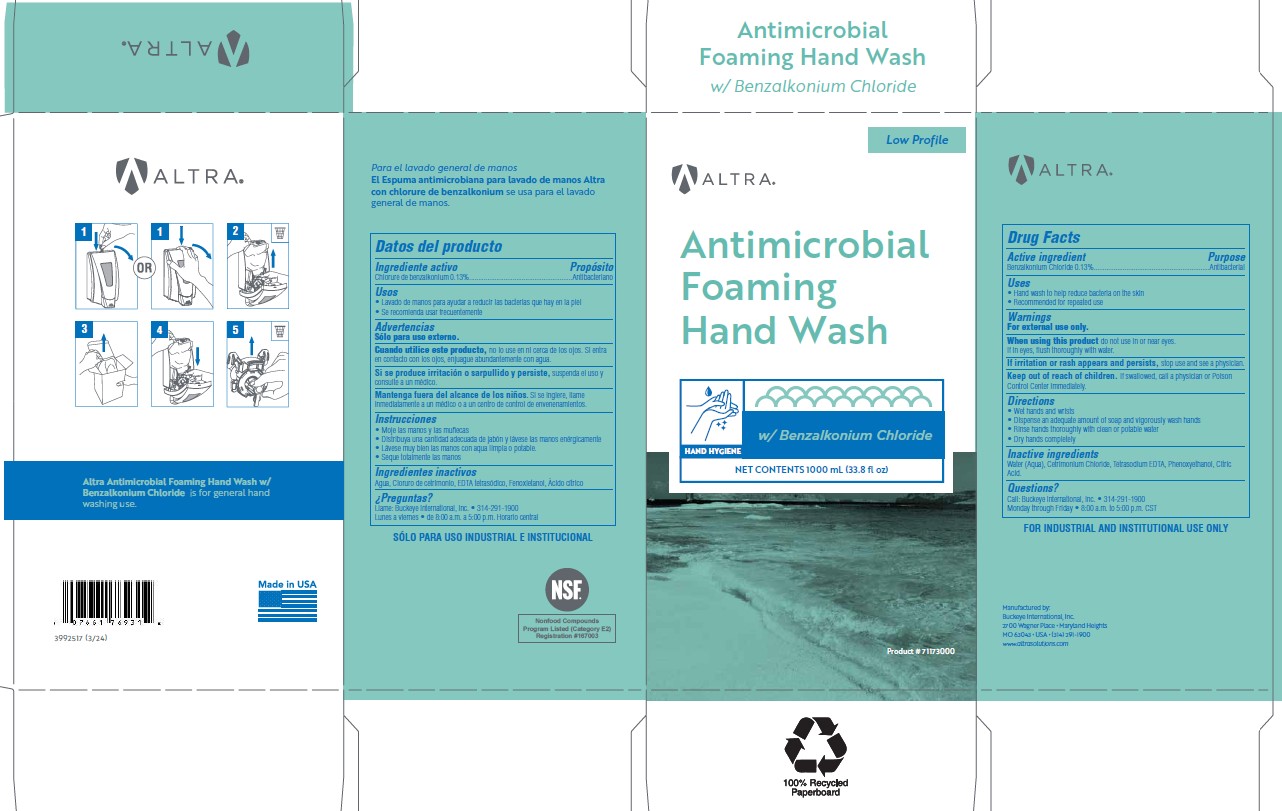 DRUG LABEL: Altra Antimicrobial Foaming Hand Wash w/ Benzalkonium Chloride
NDC: 30805-018 | Form: SOLUTION
Manufacturer: Buckeye International, Inc.
Category: otc | Type: HUMAN OTC DRUG LABEL
Date: 20241104

ACTIVE INGREDIENTS: BENZALKONIUM CHLORIDE 0.13 g/100 mL
INACTIVE INGREDIENTS: PHENOXYETHANOL; CITRIC ACID MONOHYDRATE; WATER; TETRASODIUM EDTA; CETRIMONIUM CHLORIDE

Drug Facts
30805-018

Active ingredient

Benzalkonium Chloride 0.13%

Purpose

Antibacterial

Uses

- Hand wash to help reduce bacteria on skin
- Recommended for repeated use

Warnings

For external use only.

When using this product do not use in or near eyes.

If in eyes, flush thoroughly with water.

STOP USE

If irritation or rash appears and persists, stop use and see a physician.

Keep out of reach of children. If swallowed, call a physician or Poison Control Center immediately.

Directions

- Wet hands and wrists
- Dispense an adequate amount of soap and vigorously wash hands
- Rinse hands thoroughly with clean or potable water
- Dry hands completely

Inactive ingredients

Water (Aqua), Cetrimonium Chloride, Tetrasodium EDTA, Phenoxyethanol, Citric Acid.

Questions?

Call: Buckeye International, Inc. 314-291-1900

Monday through Friday 8:00 a.m. to 5:00 p.m. CST

PACKAGE LABEL

Low Profile

ALTRA

Antimicrobial

Foaming

Hand Wash

w/ Benzalkonium Chloride

Hand Hygiene

NET CONTENTS 1000 mL (33.8 fl oz)